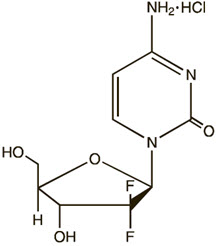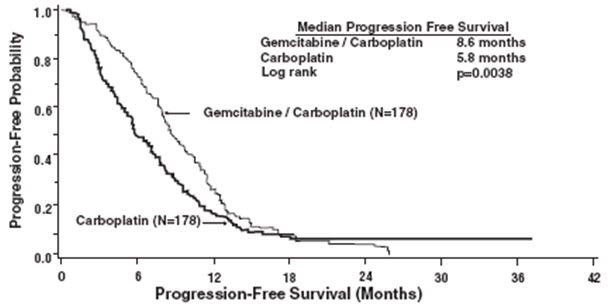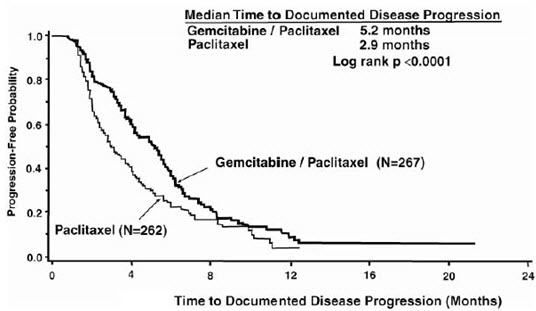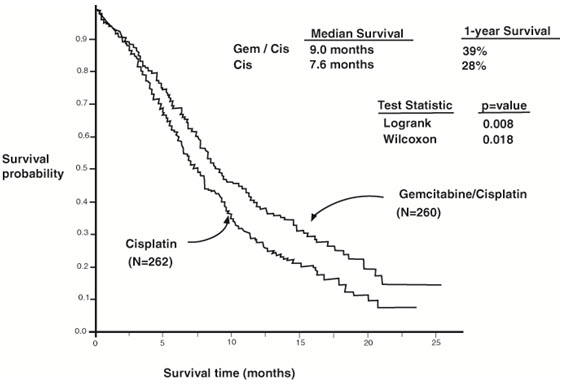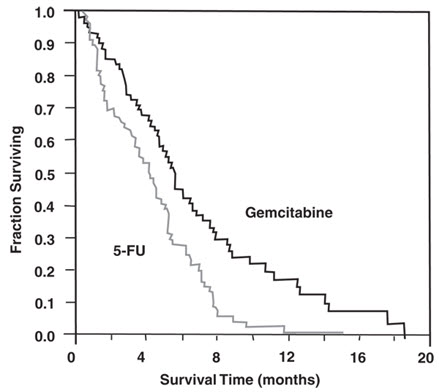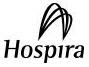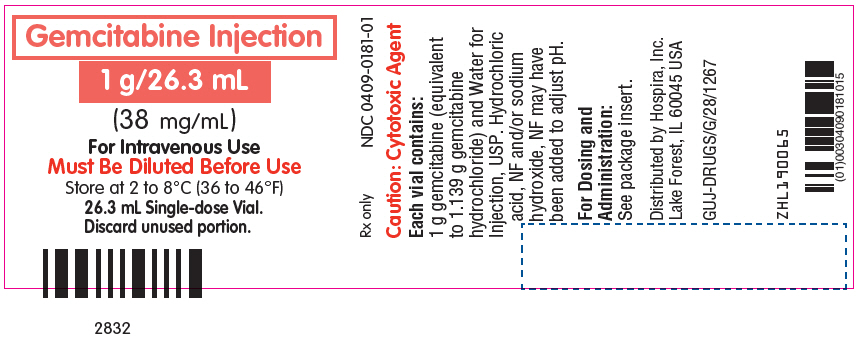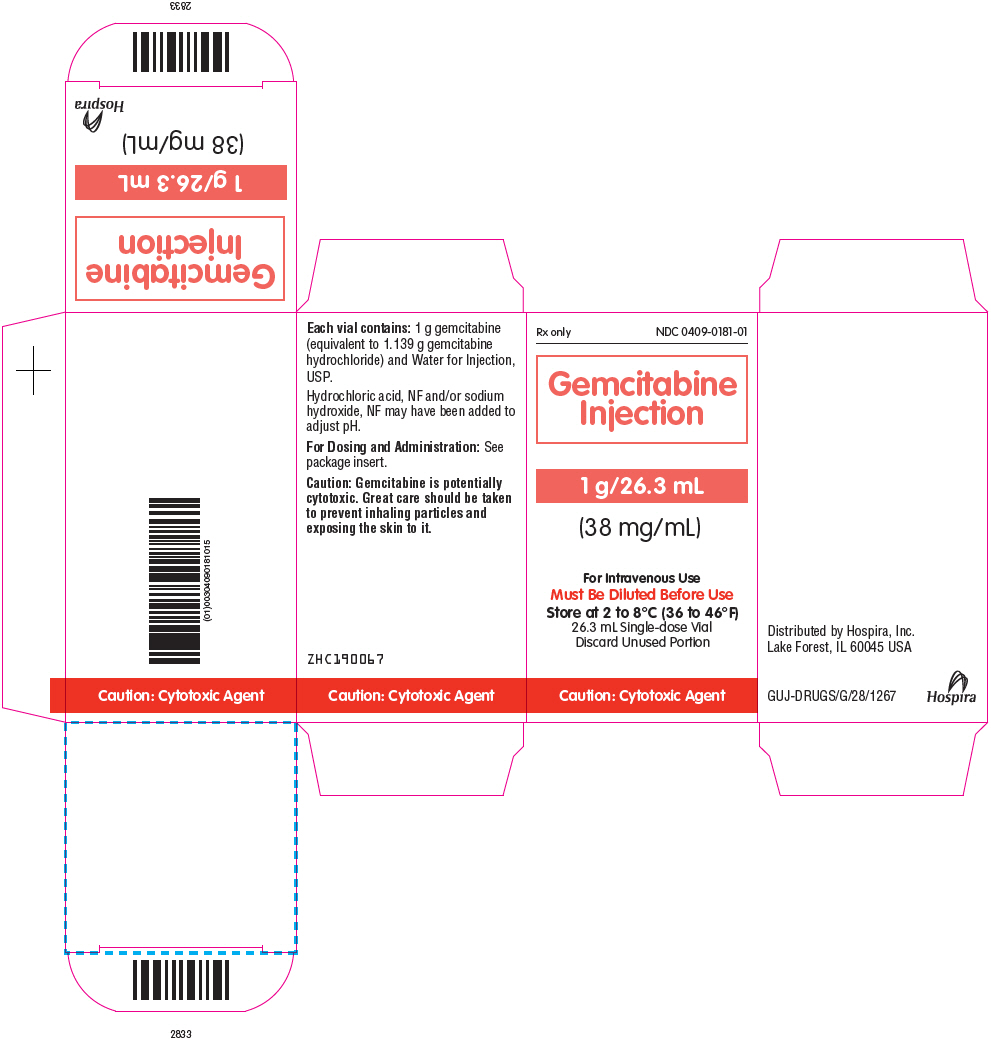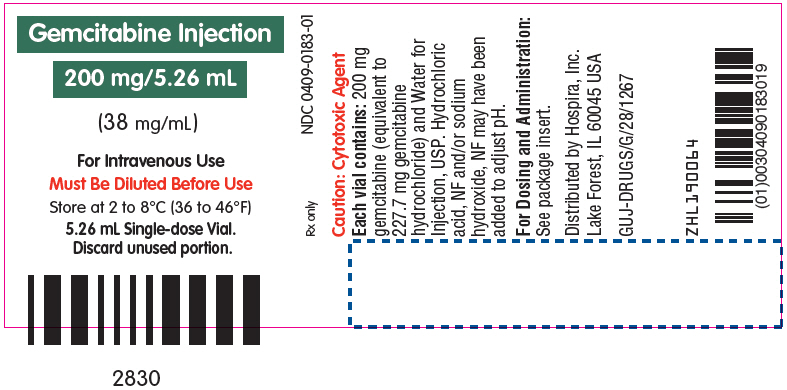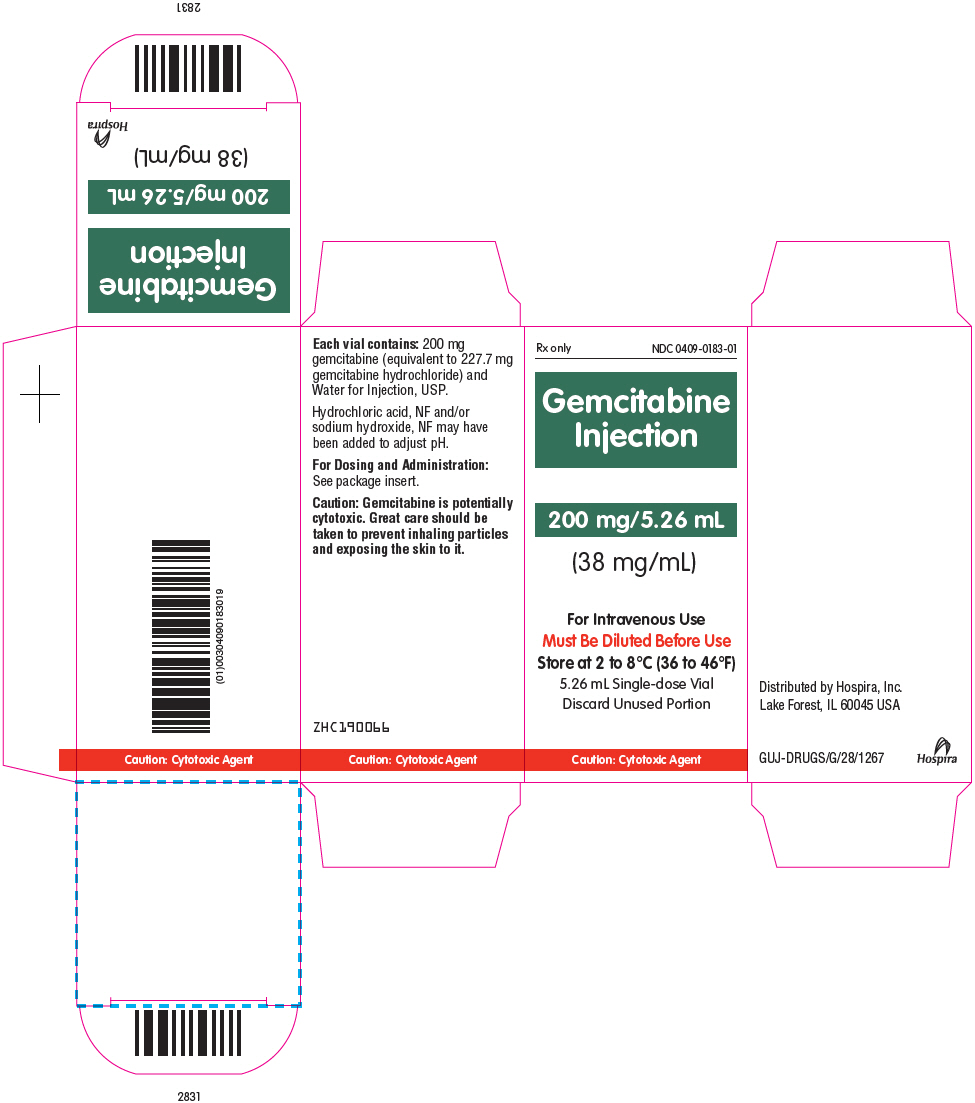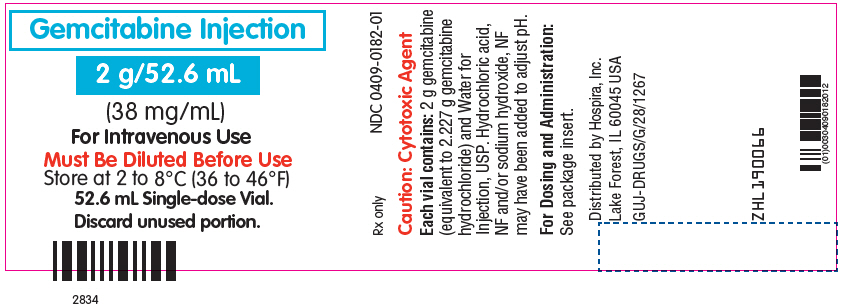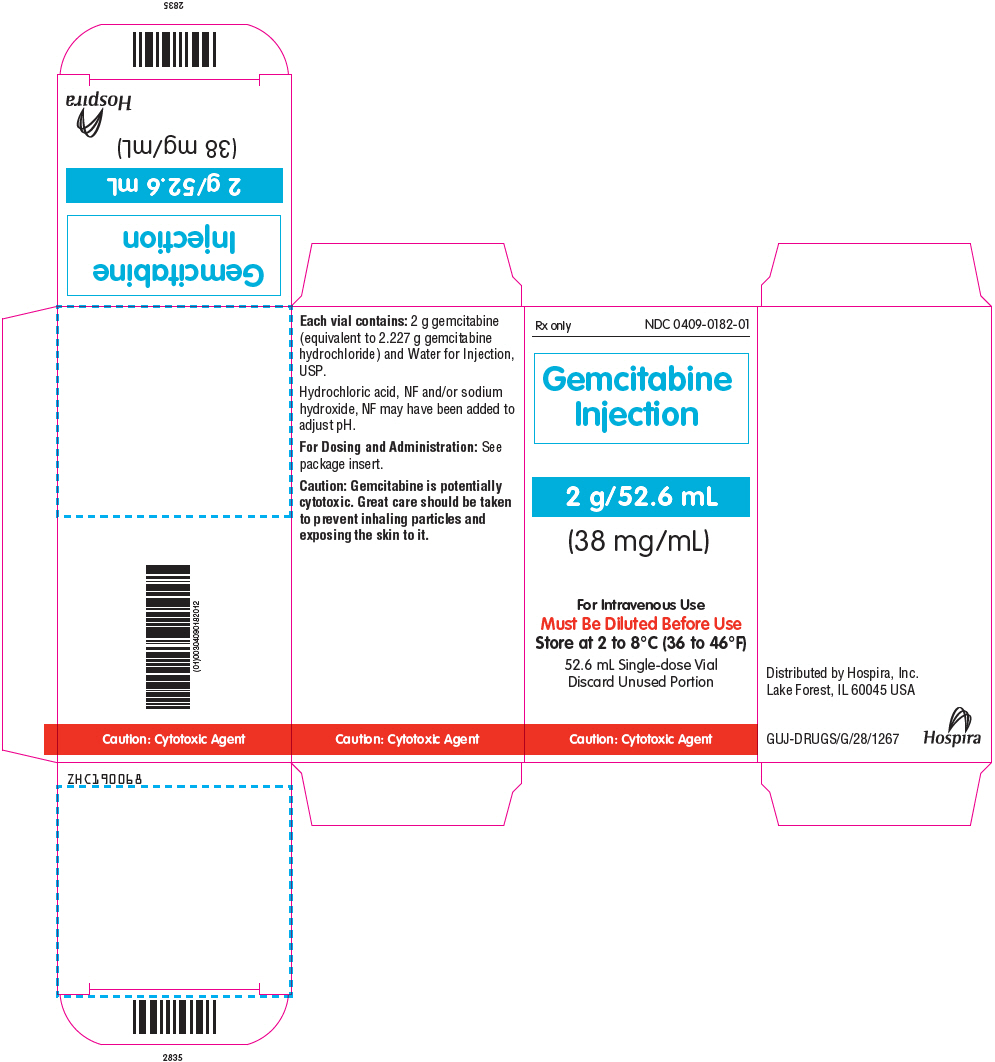 DRUG LABEL: Gemcitabine
NDC: 0409-0181 | Form: INJECTION, SOLUTION
Manufacturer: Hospira, Inc.
Category: prescription | Type: HUMAN PRESCRIPTION DRUG LABEL
Date: 20251127

ACTIVE INGREDIENTS: GEMCITABINE HYDROCHLORIDE 38 mg/1 mL
INACTIVE INGREDIENTS: WATER; HYDROCHLORIC ACID; SODIUM HYDROXIDE

HIGHLIGHTS OF PRESCRIBING INFORMATION

These highlights do not include all the information needed to use GEMCITABINE INJECTION safely and effectively. See full prescribing information for GEMCITABINE INJECTION.
GEMCITABINE injection, for intravenous use
Initial U.S. Approval: 1996

RECENT MAJOR CHANGES

Warnings and Precautions, Severe Cutaneous Adverse Reactions (5.3) | 5/2024

1 INDICATIONS AND USAGE

Gemcitabine Injection is a nucleoside metabolic inhibitor indicated:

- in combination with carboplatin, for the treatment of advanced ovarian cancer that has relapsed at least 6 months after completion of platinum-based therapy. (1.1)
- in combination with paclitaxel, for first-line treatment of metastatic breast cancer after failure of prior anthracycline-containing adjuvant chemotherapy, unless anthracyclines were clinically contraindicated. (1.2)
- in combination with cisplatin for the treatment of non-small cell lung cancer. (1.3)
- as a single agent for the treatment of pancreatic cancer. (1.4)

2 DOSAGE AND ADMINISTRATION

Gemcitabine Injection is for intravenous use only.

- Ovarian Cancer: 1000 mg/m^2 over 30 minutes on Days 1 and 8 of each 21-day cycle. (2.1)
- Breast Cancer: 1250 mg/m^2 over 30 minutes on Days 1 and 8 of each 21-day cycle. (2.2)
- Non-Small Cell Lung Cancer: 1000 mg/m^2 over 30 minutes on Days 1, 8, and 15 of each 28-day cycle or 1250 mg/m^2 over 30 minutes on Days 1 and 8 of each 21-day cycle. (2.3)
- Pancreatic Cancer: 1000 mg/m^2 over 30 minutes once weekly for the first 7 weeks, then one-week rest, then once weekly for 3 weeks of each 28-day cycle. (2.4)

3 DOSAGE FORMS AND STRENGTHS

Injection: 200 mg/5.26 mL (38 mg/mL), 1 g/26.3 mL (38 mg/mL), or 2 g/52.6 mL (38 mg/mL) in a single-dose vial. (3)

4 CONTRAINDICATIONS

Patients with a known hypersensitivity to gemcitabine. (4)

5 WARNINGS AND PRECAUTIONS

- Schedule-Dependent Toxicity: Increased toxicity with infusion time greater than 60 minutes or dosing more frequently than once weekly. (5.1)
- Myelosuppression: Monitor for myelosuppression prior to each cycle and reduce or withhold dose for severe myelosuppression. (5.2)
- Severe Cutaneous Adverse Reactions (SCARs): Permanently discontinue Gemcitabine Injection if SCARs occur. (5.3)
- Pulmonary Toxicity and Respiratory Failure: Discontinue Gemcitabine Injection for unexplained dyspnea or other evidence of severe pulmonary toxicity. (5.4)
- Hemolytic Uremic Syndrome (HUS): Monitor renal function prior to initiation and during treatment. Discontinue Gemcitabine Injection for HUS or severe renal impairment. (5.5)
- Hepatic Toxicity: Monitor hepatic function prior to initiation and during treatment. Discontinue Gemcitabine Injection for severe hepatic toxicity. (5.6)
- Embryo-Fetal Toxicity: Can cause fetal harm. Advise females and males of reproductive potential to use effective contraception. (5.7, 8.1)
- Exacerbation of Radiation Therapy Toxicity: May cause severe and life-threatening toxicity when administered during or within 7 days of radiation therapy. (5.8)
- Capillary Leak Syndrome: Discontinue Gemcitabine Injection. (5.9)
- Posterior Reversible Encephalopathy Syndrome (PRES): Discontinue Gemcitabine Injection. (5.10)

6 ADVERSE REACTIONS

The most common adverse reactions for the single agent (≥20%) are nausea/vomiting, anemia, increased aspartate aminotransferase (AST), increased alanine aminotransferase (ALT), neutropenia, increased alkaline phosphatase, proteinuria, fever, hematuria, rash, thrombocytopenia, dyspnea, and edema. (6.1)

To report SUSPECTED ADVERSE REACTIONS, contact Hospira, Inc. at 1-800-441-4100 or FDA at 1-800-FDA-1088 or www.fda.gov/medwatch.

8 USE IN SPECIFIC POPULATIONS

Lactation: Advise not to breastfeed. (8.2)

FULL PRESCRIBING INFORMATION

1 INDICATIONS AND USAGE

1.1 Ovarian Cancer

Gemcitabine Injection in combination with carboplatin is indicated for the treatment of patients with advanced ovarian cancer that has relapsed at least 6 months after completion of platinum-based therapy.

1.2 Breast Cancer

Gemcitabine Injection in combination with paclitaxel is indicated for the first-line treatment of patients with metastatic breast cancer after failure of prior anthracycline-containing adjuvant chemotherapy, unless anthracyclines were clinically contraindicated.

1.3 Non-Small Cell Lung Cancer

Gemcitabine Injection in combination with cisplatin is indicated for the first-line treatment of patients with inoperable, locally advanced (Stage IIIA or IIIB) or metastatic (Stage IV) non-small cell lung cancer (NSCLC).

1.4 Pancreatic Cancer

Gemcitabine Injection is indicated as first-line treatment for patients with locally advanced (nonresectable Stage II or Stage III) or metastatic (Stage IV) adenocarcinoma of the pancreas. Gemcitabine Injection is indicated for patients previously treated with fluorouracil.

2 DOSAGE AND ADMINISTRATION

2.1 Ovarian Cancer

Recommended Dose and Schedule

The recommended dosage of Gemcitabine Injection is 1000 mg/m^2 intravenously over 30 minutes on Days 1 and 8 of each 21-day cycle, in combination with carboplatin AUC 4 administered intravenously on Day 1 after Gemcitabine Injection administration. Refer to carboplatin prescribing information for additional information.

Dosage Modifications

Recommended dosage modifications for Gemcitabine Injection for myelosuppression are described in Tables 1 and 2 [see Warnings and Precautions (5.2)]. Refer to the recommended dosage modifications for non-hematologic adverse reactions [see Dosage and Administration (2.5)].

Table 1: Recommended Dosage Modifications for Gemcitabine Injection for Myelosuppression on Day of Treatment in Ovarian Cancer
Treatment Day | Absolute Neutrophil Count (× 10^6/L) |  | Platelet Count (× 10^6/L) | Dosage Modification
Day 1 | Greater than or equal to 1500 | And | Greater than or equal to 100,000 | None
Day 1 | Less than 1500 | Or | Less than 100,000 | Delay Treatment Cycle
Day 8 | Greater than or equal to 1500 | And | Greater than or equal to 100,000 | None
Day 8 | 1000 to 1499 | Or | 75,000 to 99,999 | 50% of full dose
Day 8 | Less than 1000 | Or | Less than 75,000 | Hold

Table 2: Recommended Dosage Modifications for Gemcitabine Injection for Myelosuppression in Previous Cycle in Ovarian Cancer
Occurrence | Myelosuppression During Treatment Cycle | Dosage Modification
Initial Occurrence | - Absolute neutrophil count less than 500 × 10^6/L for more than 5 days or - Absolute neutrophil count less than 100 × 10^6/L for more than 3 days or - Febrile neutropenia or - Platelets less than 25,000 × 10^6/L or - Cycle delay for more than one week due to toxicity | Permanently reduce Gemcitabine Injection to 800 mg/m^2 on Days 1 and 8
Subsequent Occurrence | If any of the above toxicities occur after the initial dose reduction | Permanently reduce Gemcitabine Injection dose to 800 mg/m^2 on Day 1 only

2.2 Breast Cancer

Recommended Dose and Schedule

The recommended dosage of Gemcitabine Injection is 1250 mg/m^2 intravenously over 30 minutes on Days 1 and 8 of each 21-day cycle in combination with paclitaxel 175 mg/m^2 administered as a 3-hour intravenous infusion on Day 1 before Gemcitabine Injection administration. Refer to paclitaxel prescribing information for additional information.

Dosage Modifications

Recommended dosage modifications for Gemcitabine Injection for myelosuppression are described in Table 3 [see Warnings and Precautions (5.2)]. Refer to the recommended dosage modifications for non-hematologic adverse reactions [see Dosage and Administration (2.5)].

Table 3: Recommended Dosage Modifications for Gemcitabine Injection for Myelosuppression on Day of Treatment in Breast Cancer
Treatment Day | Absolute Neutrophil Count (× 10^6/L) |  | Platelet Count (× 10^6/L) | Dosage Modification
Day 1 | Greater than or equal to 1500 | And | Greater than or equal to 100,000 | None
Day 1 | Less than 1500 | Or | Less than 100,000 | Hold
Day 8 | Greater than or equal to 1200 | And | Greater than 75,000 | None
Day 8 | 1000 to 1199 | Or | 50,000 to 75,000 | 75% of full dose
Day 8 | 700 to 999 | And | Greater than or equal to 50,000 | 50% of full dose
Day 8 | Less than 700 | Or | Less than 50,000 | Hold

2.3 Non-Small Cell Lung Cancer

Recommended Dose and Schedule

28-day schedule

The recommended dosage of Gemcitabine Injection is 1000 mg/m^2 intravenously over 30 minutes on Days 1, 8, and 15 of each 28-day cycle in combination with cisplatin 100 mg/m^2 administered intravenously on Day 1 after Gemcitabine Injection administration.

21-day schedule

The recommended dosage of Gemcitabine Injection is 1250 mg/m^2 intravenously over 30 minutes on Days 1 and 8 of each 21-day cycle in combination with cisplatin 100 mg/m^2 administered intravenously on Day 1 after Gemcitabine Injection administration.

Refer to cisplatin prescribing information for additional information.

Dosage Modifications

Recommended dosage modifications for Gemcitabine Injection myelosuppression are described in Table 4 [see Warnings and Precautions (5.2)]. Refer to the recommended dosage modifications for non-hematologic adverse reactions [see Dosage and Administration (2.5)].

2.4 Pancreatic Cancer

Recommended Dose and Schedule

The recommended dosage of Gemcitabine Injection is 1000 mg/m^2 intravenously over 30 minutes. The recommended treatment schedule is as follows:

- Weeks 1 to 8: weekly dosing for the first 7 weeks followed by one-week rest.
- After week 8: weekly dosing on Days 1, 8, and 15 of each 28-day cycle.

Dosage Modifications

Recommended dosage modifications for Gemcitabine Injection for myelosuppression are described in Table 4 [see Warnings and Precautions (5.2)]. Refer to the recommended dosage modifications for non-hematologic adverse reactions [see Dosage and Administration (2.5)].

Table 4: Recommended Dosage Modifications for Gemcitabine Injection for Myelosuppression in Pancreatic Cancer and Non-Small Cell Lung Cancer
Absolute Neutrophil Count (× 10^6/L) |  | Platelet Count (× 10^6/L) | Dosage Modification
Greater than or equal to 1000 | And | Greater than or equal to 100,000 | None
500 to 999 | Or | 50,000 to 99,999 | 75% of full dose
Less than 500 | Or | Less than 50,000 | Hold

2.5 Dosage Modifications for Non-Hematologic Adverse Reactions

Permanently discontinue Gemcitabine Injection for any of the following:

- Severe Cutaneous Adverse Reactions (SCARs) [see Warnings and Precautions (5.3)]
- Unexplained dyspnea or evidence of severe pulmonary toxicity [see Warnings and Precautions (5.4)]
- Hemolytic uremic syndrome (HUS) or severe renal impairment [see Warnings and Precautions (5.5)]
- Severe hepatic toxicity [see Warnings and Precautions (5.6)]
- Capillary leak syndrome (CLS) [see Warnings and Precautions (5.9)]
- Posterior reversible encephalopathy syndrome (PRES) [see Warnings and Precautions (5.10)]

Withhold Gemcitabine Injection or reduce dose by 50% for other Grade 3 or 4 non-hematological adverse reactions until resolved. No dose modifications are recommended for alopecia, nausea, or vomiting.

2.6 Preparation

Gemcitabine Injection is a cytotoxic drug. Follow applicable special handling and disposal procedures.^1

Exercise caution and wear gloves when preparing Gemcitabine Injection solutions. Immediately wash the skin thoroughly or rinse the mucosa with copious amounts of water if Gemcitabine Injection contacts the skin or mucus membranes. Death has occurred in animal studies due to dermal absorption.

Preparation for Intravenous Infusion Administration

- Withdraw the calculated dose from the vial and discard any unused portion.
- Prior to administration, dilute the appropriate amount of drug with 0.9% Sodium Chloride Injection to a minimum final concentration of at least 0.1 mg/mL.
- Store diluted Gemcitabine Injection solution for no more than 24 hours at controlled room temperature of 20° to 25°C (68° to 77°F) [see USP Controlled Room Temperature]. Discard if not used within 24 hours after dilution.
- Visually inspect for particulate matter or discoloration prior to administration and discard if particulate matter or discoloration is observed.
- No incompatibilities have been observed with infusion bottles or polyvinyl chloride bags and administration sets.

3 DOSAGE FORMS AND STRENGTHS

Injection: 200 mg/5.26 mL (38 mg/mL), 1 g/26.3 mL (38 mg/mL), and 2 g/52.6 mL (38 mg/mL) as a clear and colorless to light straw-colored solution in a single-dose vial.

4 CONTRAINDICATIONS

Gemcitabine Injection is contraindicated in patients with a known hypersensitivity to gemcitabine. Reactions include anaphylaxis [see Adverse Reactions (6. 1)].

5 WARNINGS AND PRECAUTIONS

5.1 Schedule-Dependent Toxicity

In clinical trials evaluating the maximum tolerated dose of gemcitabine, prolongation of the infusion time beyond 60 minutes or more frequent than weekly dosing resulted in an increased incidence of clinically significant hypotension, severe flu-like symptoms, myelosuppression, and asthenia. The half-life of gemcitabine is influenced by the length of the infusion [see Clinical Pharmacology (12.3)]. Refer to the recommended Gemcitabine Injection dosage [see Dosage and Administration (2.1, 2.2, 2.3, 2.4)].

5.2 Myelosuppression

Myelosuppression manifested by neutropenia, thrombocytopenia, and anemia, occurs with gemcitabine as a single agent and the risks are increased when gemcitabine is combined with other cytotoxic drugs. In clinical trials, Grade 3–4 neutropenia, anemia, and thrombocytopenia occurred in 25%, 8%, and 5%, respectively of the 979 patients who received single agent gemcitabine. The frequencies of Grade 3–4 neutropenia, anemia, and thrombocytopenia varied from 48% to 71%, 8% to 28%, and 5% to 55%, respectively, in patients receiving gemcitabine in combination with another drug [see Adverse Reactions (6.1)].

Prior to each dose of Gemcitabine Injection, obtain a complete blood count (CBC) with a differential and a platelet count. Modify the dosage as recommended [see Dosage and Administration (2.1, 2.2, 2.3, 2.4)].

5.3 Severe Cutaneous Adverse Reactions (SCARs)

SCARs, including Stevens-Johnson syndrome (SJS), toxic epidermal necrolysis (TEN), drug reaction with eosinophilia and systemic symptoms (DRESS), and acute generalized exanthematous pustulosis (AGEP), which can be life-threatening or fatal, have been reported in association with gemcitabine treatment [see Adverse Reactions (6.2)]. Monitor patients for signs and symptoms of severe cutaneous adverse reactions. Permanently discontinue gemcitabine in patients who develop SCARs.

5.4 Pulmonary Toxicity and Respiratory Failure

Pulmonary toxicity, including interstitial pneumonitis, pulmonary fibrosis, pulmonary edema, and adult respiratory distress syndrome (ARDS), has been reported. In some cases, these pulmonary events can lead to fatal respiratory failure despite the discontinuation of therapy. The onset of pulmonary symptoms may occur up to 2 weeks after the last dose of gemcitabine [see Adverse Reactions (6.1, 6.2)].

Permanently discontinue Gemcitabine Injection in patients who develop unexplained dyspnea, with or without bronchospasm, or evidence of severe pulmonary toxicity.

5.5 Hemolytic Uremic Syndrome

Hemolytic uremic syndrome (HUS), including fatalities from renal failure or the requirement for dialysis, can occur with gemcitabine. In clinical trials, HUS occurred in 0.25% of 2429 patients. Most fatal cases of renal failure were due to HUS [see Adverse Reactions (6.1)]. Serious cases of thrombotic microangiopathy (TMA) other than HUS have been reported with gemcitabine [see Adverse Reactions (6.2)].

Assess renal function prior to initiation of Gemcitabine Injection and periodically during treatment. Consider the diagnosis of HUS in patients who develop anemia with evidence of microangiopathic hemolysis; increased bilirubin or LDH; reticulocytosis; severe thrombocytopenia; or evidence of renal failure (increased serum creatinine or BUN). Permanently discontinue Gemcitabine Injection in patients with HUS or severe renal impairment. Renal failure may not be reversible even with the discontinuation of therapy.

5.6 Hepatic Toxicity

Drug-induced liver injury, including liver failure and death, has been reported in patients receiving gemcitabine alone or with other potentially hepatotoxic drugs [see Adverse Reactions (6.1, 6.2)]. Administration of gemcitabine in patients with concurrent liver metastases or a pre-existing medical history of hepatitis, alcoholism, or liver cirrhosis can lead to exacerbation of the underlying hepatic insufficiency.

Assess hepatic function prior to initiation of Gemcitabine Injection and periodically during treatment. Permanently discontinue Gemcitabine Injection in patients who develop severe hepatic toxicity.

5.7 Embryo-Fetal Toxicity

Based on animal data and its mechanism of action, Gemcitabine Injection can cause fetal harm when administered to a pregnant woman. Gemcitabine was teratogenic, embryotoxic, and fetotoxic in mice and rabbits.

Advise pregnant women of the potential risk to a fetus.

Advise females of reproductive potential to use effective contraception during treatment with Gemcitabine Injection and for 6 months after the final dose. Advise male patients with female partners of reproductive potential to use effective contraception during treatment with Gemcitabine Injection and for 3 months following the final dose [see Use in Specific Populations (8.1, 8.3)].

5.8 Exacerbation of Radiation Therapy Toxicity

Gemcitabine is not recommended for use in combination with radiation therapy.

Concurrent (given together or ≤7 days apart)

Life-threatening mucositis, especially esophagitis and pneumonitis occurred in a trial in which gemcitabine was administered at a dose of 1000 mg/m^2 to patients with non-small cell lung cancer for up to 6 consecutive weeks concurrently with thoracic radiation.

Non-Concurrent (given >7 days apart)

Excessive toxicity has not been observed when gemcitabine is administered more than 7 days before or after radiation. Radiation recall has been reported in patients who received gemcitabine after prior radiation.

5.9 Capillary Leak Syndrome

Capillary leak syndrome (CLS) with severe consequences has been reported in patients receiving gemcitabine as a single agent or in combination with other chemotherapeutic agents [see Adverse Reactions (6.2)]. Permanently discontinue Gemcitabine Injection if CLS develops during therapy.

5.10 Posterior Reversible Encephalopathy Syndrome

Posterior reversible encephalopathy syndrome (PRES) has been reported in patients receiving gemcitabine as a single agent or in combination with other chemotherapeutic agents [see Adverse Reactions (6.2)]. PRES can present with headache, seizure, lethargy, hypertension, confusion, blindness, and other visual and neurologic disturbances. Confirm the diagnosis of PRES with magnetic resonance imaging (MRI). Permanently discontinue Gemcitabine Injection if PRES develops during therapy.

6 ADVERSE REACTIONS

The following clinically significant adverse reactions are described elsewhere in the labeling:

- Hypersensitivity [see Contraindications (4)]
- Schedule-Dependent Toxicity [see Warnings and Precautions (5.1)]
- Myelosuppression [see Warnings and Precautions (5.2)]
- Severe Cutaneous Adverse Reactions [see Warnings and Precautions (5.3)]
- Pulmonary Toxicity and Respiratory Failure [see Warnings and Precautions (5.4)]
- Hemolytic Uremic Syndrome [see Warnings and Precautions (5.5)]
- Hepatic Toxicity [see Warnings and Precautions (5.6)]
- Exacerbation of Radiation Therapy Toxicity [see Warnings and Precautions (5.8)]
- Capillary Leak Syndrome [see Warnings and Precautions (5.9)]
- Posterior Reversible Encephalopathy Syndrome [see Warnings and Precautions (5.10)]

6.1 Clinical Trials Experience

Because clinical trials are conducted under widely varying conditions, adverse reaction rates observed in the clinical trials of a drug cannot be directly compared to rates in the clinical trials of another drug and may not reflect the rates observed in practice.

Single Agent

The data described below reflect exposure to gemcitabine as a single agent administered at doses between 800 mg/m^2 to 1250 mg/m^2 intravenously over 30 minutes once weekly, in 979 patients with various malignancies. The most common (≥20%) adverse reactions of single agent gemcitabine are nausea/vomiting, anemia, increased alanine aminotransferase (ALT), increased aspartate aminotransferase (AST), neutropenia, increased alkaline phosphatase, proteinuria, fever, hematuria, rash, thrombocytopenia, dyspnea, and edema. The most common (≥5%) Grade 3 or 4 adverse reactions were neutropenia, nausea/vomiting, increased ALT, increased alkaline phosphatase, anemia, increased AST, and thrombocytopenia. Approximately 10% of the 979 patients discontinued gemcitabine due to adverse reactions. Adverse reactions resulting in discontinuation of gemcitabine in 2% of 979 patients were cardiovascular adverse reactions (myocardial infarction, cerebrovascular accident, arrhythmia, and hypertension) and adverse reactions resulting in discontinuation of gemcitabine in <1% of 979 patients were anemia, thrombocytopenia, hepatic dysfunction, renal dysfunction, nausea/vomiting, fever, rash, dyspnea, hemorrhage, infection, stomatitis, somnolence, flu-like syndrome, and edema.

Tables 5 and 6 present the incidence of selected adverse reactions and laboratory abnormalities reported in patients with various malignancies receiving single agent gemcitabine across 5 clinical trials. Additional clinically significant adverse reactions are provided following Table 6.

Table 5: Selected Adverse Reactions Occurring in ≥10% of Patients Receiving Single Agent Gemcitabine [Grade based on criteria from the World Health Organization (WHO).]
Adverse Reactions [For approximately 60% of patients, non-laboratory adverse events were graded only if assessed to be possibly drug-related.] | Gemcitabine [N=699–974; all patients with laboratory or non-laboratory data.]
 | All Grades (%) | Grade 3 (%) | Grade 4 (%)
Nausea and Vomiting | 69 | 13 | 1
Fever | 41 | 2 | 0
Rash | 30 | <1 | 0
Dyspnea | 23 | 3 | <1
Diarrhea | 19 | 1 | 0
Hemorrhage | 17 | <1 | <1
Infection | 16 | 1 | <1
Alopecia | 15 | <1 | 0
Stomatitis | 11 | <1 | 0
Somnolence | 11 | <1 | <1
Paresthesias | 10 | <1 | 0

Table 6: Selected Laboratory Abnormalities Occurring in Patients Receiving Single Agent Gemcitabine [Grade based on criteria from WHO.]
Laboratory Abnormality [Regardless of causality.] | Gemcitabine [N=699–974; all patients with laboratory or non-laboratory data.]
 | All Grades (%) | Grade 3 (%) | Grade 4 (%)
Hematologic
Anemia | 68 | 7 | 1
Neutropenia | 63 | 19 | 6
Thrombocytopenia | 24 | 4 | 1
Hepatic
Increased ALT | 68 | 8 | 2
Increased AST | 67 | 6 | 2
Increased Alkaline Phosphatase | 55 | 7 | 2
Hyperbilirubinemia | 13 | 2 | <1
Renal
Proteinuria | 45 | <1 | 0
Hematuria | 35 | <1 | 0
Increased BUN | 16 | 0 | 0
Increased Creatinine | 8 | <1 | 0

Additional adverse reactions include the following:

- Transfusion requirements: Red blood cell transfusions (19%); platelet transfusions (<1%)
- Edema: Edema (13%), peripheral edema (20%), generalized edema (<1%)
- Flu-like symptoms: Fever, asthenia, anorexia, headache, cough, chills, myalgia, insomnia, rhinitis, sweating, and/or malaise (19%)
- Infection: Sepsis (<1%)
- Extravasation: Injection-site reactions (4%)
- Allergic: Bronchospasm (<2%); anaphylactoid reactions

Ovarian Cancer

Tables 7 and 8 present the incidence of selected adverse reactions and laboratory abnormalities, occurring in ≥10% of gemcitabine-treated patients and at a higher incidence in the gemcitabine/carboplatin arm, reported in a randomized trial (Study 1) of gemcitabine with carboplatin (n=175) compared to carboplatin alone (n=174) for the second-line treatment of ovarian cancer in women with disease that had relapsed more than 6 months following first-line platinum-based chemotherapy [see Clinical Studies (14.1)]. Additional clinically significant adverse reactions, occurring in <10% of patients, are provided following Table 8.

The proportion of patients with dose adjustments for carboplatin (1.8% versus 3.8%), doses of carboplatin omitted (0.2% versus 0) and discontinuing treatment for adverse reactions (11% versus 10%), were similar between arms. Dose adjustment for gemcitabine occurred in 10% of patients and gemcitabine dose was omitted in 14% of patients in the gemcitabine/carboplatin arm.

Table 7: Adverse Reactions Occurring in >10% of Patients Receiving Gemcitabine with Carboplatin and at Higher Incidence than in Patients Receiving Single Agent Carboplatin [Between Arm Difference of ≥5% (All Grades) or ≥2% (Grades 3–4)] in Study 1 [Grade based on National Cancer Institute Common Toxicity Criteria (CTC) Version 2.0.]
Adverse Reactions [Regardless of causality.] | Gemcitabine/Carboplatin (N=175) |  |  | Carboplatin (N=174)
 | All Grades (%) | Grade 3 (%) | Grade 4 (%) | All Grades (%) | Grade 3 (%) | Grade 4 (%)
Nausea | 69 | 6 | 0 | 61 | 3 | 0
Alopecia | 49 | 0 | 0 | 17 | 0 | 0
Vomiting | 46 | 6 | 0 | 36 | 2 | <1
Constipation | 42 | 6 | 1 | 37 | 3 | 0
Fatigue | 40 | 3 | <1 | 32 | 5 | 0
Diarrhea | 25 | 3 | 0 | 14 | <1 | 0
Stomatitis/Pharyngitis | 22 | <1 | 0 | 13 | 0 | 0

Table 8: Laboratory Abnormalities Occurring in Patients Receiving Gemcitabine with Carboplatin and at Higher Incidence than in Patients Receiving Single Agent Carboplatin [Between Arm Difference of ≥5% (All Grades) or ≥2% (Grades 3–4)] in Study 1 [Grade based on National Cancer Institute CTC Version 2.0.]
Laboratory Abnormality [Regardless of causality.] | Gemcitabine/Carboplatin (N=175) |  |  | Carboplatin (N=174)
 | All Grades (%) | Grade 3 (%) | Grade 4 (%) | All Grades (%) | Grade 3 (%) | Grade 4 (%)
Hematologic
Neutropenia | 90 | 42 | 29 | 58 | 11 | 1
Anemia | 86 | 22 | 6 | 75 | 9 | 2
Thrombocytopenia | 78 | 30 | 5 | 57 | 10 | 1
RBC Transfusion [Percent of patients receiving transfusions. Transfusions are not CTC-graded events. Blood transfusions included both packed red blood cells and whole blood.] | 38 | - | - | 15 | - | -
Platelet Transfusion | 9 | - | - | 3 | - | -

Hematopoietic growth factors were administered more frequently in the gemcitabine-containing arm: leukocyte growth factor (24% and 10%) and erythropoiesis-stimulating agent (7% and 3.9%).

The following clinically relevant, Grade 3 and 4 adverse reactions occurred more frequently in the gemcitabine with carboplatin arm: dyspnea (3.4% versus 2.9%), febrile neutropenia (1.1% versus 0), hemorrhagic event (2.3% versus 1.1%), motor neuropathy (1.1% versus 0.6%), and rash/desquamation (0.6% versus 0).

Breast Cancer

Tables 9 and 10 present the incidence of selected adverse reactions and laboratory abnormalities, occurring in ≥10% of gemcitabine-treated patients and at a higher incidence in the gemcitabine/paclitaxel arm, reported in a randomized trial (Study 2) of gemcitabine with paclitaxel (n=262) compared to paclitaxel alone (n=259) for the first-line treatment of metastatic breast cancer (MBC) in women who received anthracycline-containing chemotherapy in the adjuvant/neo-adjuvant setting or for whom anthracyclines were contraindicated [see Clinical Studies (14.2)]. Additional clinically significant adverse reactions, occurring in <10% of patients, are provided following Table 10.

The requirement for dose reduction of paclitaxel were higher for patients in the gemcitabine/paclitaxel arm (5% versus 2%). The number of paclitaxel doses omitted (<1%), the proportion of patients discontinuing treatment for adverse reactions (7% versus 5%) and the number of treatment-related deaths (1 patient in each arm) were similar between the two arms.

Table 9: Selected Adverse Reactions Occurring in Patients Receiving Gemcitabine with Paclitaxel and at Higher Incidence than in Patients Receiving Single Agent Paclitaxel [Between Arm Difference of ≥5% (All Grades) or ≥2% (Grades 3–4)] in Study 2 [Grade based on National Cancer Institute CTC Version 2.0.]
Adverse Reactions [Non-laboratory events were graded only if assessed to be possibly drug-related.] | Gemcitabine/Paclitaxel (N=262) |  |  | Paclitaxel (N=259)
 | All Grades (%) | Grade 3 (%) | Grade 4 (%) | All Grades (%) | Grade 3 (%) | Grade 4 (%)
Alopecia | 90 | 14 | 4 | 92 | 19 | 3
Neuropathy-Sensory | 64 | 5 | <1 | 58 | 3 | 0
Nausea | 50 | 1 | 0 | 31 | 2 | 0
Fatigue | 40 | 6 | <1 | 28 | 1 | <1
Vomiting | 29 | 2 | 0 | 15 | 2 | 0
Diarrhea | 20 | 3 | 0 | 13 | 2 | 0
Anorexia | 17 | 0 | 0 | 12 | <1 | 0
Neuropathy-Motor | 15 | 2 | <1 | 10 | <1 | 0
Stomatitis/Pharyngitis | 13 | 1 | <1 | 8 | <1 | 0
Fever | 13 | <1 | 0 | 3 | 0 | 0
Rash/Desquamation | 11 | <1 | <1 | 5 | 0 | 0
Febrile Neutropenia | 6 | 5 | <1 | 2 | 1 | 0

Table 10: Selected Laboratory Abnormalities Occurring in >10% of Patients Receiving Gemcitabine with Paclitaxel and at a Higher Incidence than Patients Receiving Single Agent Paclitaxel [Between Arm Difference of ≥5% (All Grades) or ≥2% (Grades 3–4)] in Study 2 [Grade based on National Cancer Institute CTC Version 2.0.]
Laboratory Abnormality [Regardless of causality.] | Gemcitabine/ Paclitaxel (N=262) |  |  | Paclitaxel (N=259)
 | All Grades (%) | Grade 3 (%) | Grade 4 (%) | All Grades (%) | Grade 3 (%) | Grade 4 (%)
Hematologic
Anemia | 69 | 6 | 1 | 51 | 3 | <1
Neutropenia | 69 | 31 | 17 | 31 | 4 | 7
Thrombocytopenia | 26 | 5 | <1 | 7 | <1 | <1
Hepatobiliary
Increased ALT | 18 | 5 | <1 | 6 | <1 | 0
Increased AST | 16 | 2 | 0 | 5 | <1 | 0

Clinically relevant Grade 3 or 4 dyspnea occurred with a higher incidence in the gemcitabine with paclitaxel arm compared with the paclitaxel arm (1.9% versus 0).

Non-Small Cell Lung Cancer

Tables 11 and 12 present the incidence of selected adverse reactions and laboratory abnormalities, occurring in ≥10% of gemcitabine-treated patients and at a higher incidence in the gemcitabine with cisplatin arm, reported in a randomized trial (Study 3) of gemcitabine with cisplatin (n=260) administered in 28-day cycles as compared to cisplatin alone (n=262) in patients receiving first-line treatment for locally advanced or metastatic NSCLC [see Clinical Studies (14.3)].

Patients randomized to gemcitabine with cisplatin received a median of 4 cycles of treatment and those randomized to cisplatin alone received a median of 2 cycles of treatment. In this trial, the requirement for dose adjustments (>90% versus 16%), discontinuation of treatment for adverse reactions (15% versus 8%), and the proportion of patients hospitalized (36% versus 23%) were all higher for patients receiving gemcitabine with cisplatin compared to those receiving cisplatin alone. The incidence of febrile neutropenia (3% versus <1%), sepsis (4% versus 1%), Grade 3 cardiac dysrhythmias (3% versus <1%) were all higher in the gemcitabine/cisplatin arm compared to the cisplatin alone arm. The two-drug combination was more myelosuppressive with 4 (1.5%) possibly treatment-related deaths, including 3 resulting from myelosuppression with infection and one case of renal failure associated with pancytopenia and infection. No deaths due to treatment were reported on the cisplatin arm.

Table 11: Selected Adverse Reactions Occurring in ≥10% of Patients Receiving Gemcitabine with Cisplatin and at Higher Incidence than in Patients Receiving Single Agent Cisplatin [Between Arm Difference of ≥5% (All Grades) or ≥2% (Grades 3–4)] in Study 3 [Grade based on National Cancer Institute CTC.]
Adverse Reactions [Non-laboratory events were graded only if assessed to be possibly drug-related.] | Gemcitabine/Cisplatin [N=217–253; all gemcitabine/cisplatin patients with laboratory or non-laboratory data.] |  |  | Cisplatin [N=213–248; all cisplatin patients with laboratory or non-laboratory data.]
 | All Grades (%) | Grade 3 (%) | Grade 4 (%) | All Grades (%) | Grade 3 (%) | Grade 4 (%)
Nausea | 93 | 25 | 2 | 87 | 20 | <1
Vomiting | 78 | 11 | 12 | 71 | 10 | 9
Alopecia | 53 | 1 | 0 | 33 | 0 | 0
Neuro Motor | 35 | 12 | 0 | 15 | 3 | 0
Diarrhea | 24 | 2 | 2 | 13 | 0 | 0
Neuro Sensory | 23 | 1 | 0 | 18 | 1 | 0
Infection | 18 | 3 | 2 | 12 | 1 | 0
Fever | 16 | 0 | 0 | 5 | 0 | 0
Neuro Cortical | 16 | 3 | 1 | 9 | 1 | 0
Neuro Mood | 16 | 1 | 0 | 10 | 1 | 0
Local | 15 | 0 | 0 | 6 | 0 | 0
Neuro Headache | 14 | 0 | 0 | 7 | 0 | 0
Stomatitis | 14 | 1 | 0 | 5 | 0 | 0
Hemorrhage | 14 | 1 | 0 | 4 | 0 | 0
Hypotension | 12 | 1 | 0 | 7 | 1 | 0
Rash | 11 | 0 | 0 | 3 | 0 | 0

Table 12: Selected Laboratory Abnormalities Occurring in >10% of Patients Receiving Gemcitabine with Cisplatin and at Higher Incidence than in Patients Receiving Single Agent Cisplatin [Between Arm Difference of ≥5% (All Grades) or ≥2% (Grades 3–4)] in Study 3 [Grade based on National Cancer Institute CTC.]
Laboratory Abnormality [Regardless of causality.] | Gemcitabine/Cisplatin [N=217–253; all gemcitabine/cisplatin patients with laboratory or non-laboratory data.] |  |  | Cisplatin [N=213–248; all cisplatin patients with laboratory or non-laboratory data.]
 | All Grades (%) | Grade 3 (%) | Grade 4 (%) | All Grades (%) | Grade 3 (%) | Grade 4 (%)
Hematologic
Anemia | 89 | 22 | 3 | 67 | 6 | 1
Thrombocytopenia | 85 | 25 | 25 | 13 | 3 | 1
Neutropenia | 79 | 22 | 35 | 20 | 3 | 1
Lymphopenia | 75 | 25 | 18 | 51 | 12 | 5
RBC Transfusion [Percent of patients receiving transfusions. Percent transfusions are not CTC-graded events.] | 39 | - | - | 13 | - | -
Platelet Transfusions | 21 | - | - | <1 | - | -
Hepatic
Increased Transaminase | 22 | 2 | 1 | 10 | 1 | 0
Increased Alkaline Phosphatase | 19 | 1 | 0 | 13 | 0 | 0
Renal
Increased Creatinine | 38 | 4 | <1 | 31 | 2 | <1
Proteinuria | 23 | 0 | 0 | 18 | 0 | 0
Hematuria | 15 | 0 | 0 | 13 | 0 | 0
Other Laboratory
Hyperglycemia | 30 | 4 | 0 | 23 | 3 | 0
Hypomagnesemia | 30 | 4 | 3 | 17 | 2 | 0
Hypocalcemia | 18 | 2 | 0 | 7 | 0 | <1

Tables 13 and 14 present the incidence of selected adverse reactions and laboratory abnormalities, occurring in ≥10% of gemcitabine-treated patients and at a higher incidence in the gemcitabine with cisplatin arm, reported in a randomized trial (Study 4) of gemcitabine with cisplatin (n=69) administered in 21-day cycles as compared to etoposide with cisplatin (n=66) in patients receiving first-line treatment for locally advanced or metastatic NSCLC [see Clinical Studies (14.3)]. Additional clinically significant adverse reactions are provided following Table 14.

Patients in the gemcitabine/cisplatin (GC) arm received a median of 5 cycles and those in the etoposide/cisplatin (EC) arm received a median of 4 cycles. The majority of patients receiving more than one cycle of treatment required dose adjustments; 81% in the GC arm and 68% in the EC arm. The incidence of hospitalizations for adverse reactions was 22% in the GC arm and 27% in the EC arm. The proportion of patients who discontinued treatment for adverse reactions was higher in the GC arm (14% versus 8%). The proportion of patients who were hospitalized for febrile neutropenia was lower in the GC arm (7% versus 12%). There was one death attributed to treatment, a patient with febrile neutropenia and renal failure, which occurred in the GC arm.

Table 13: Selected Adverse Reactions in Patients Receiving Gemcitabine with Cisplatin in Study 4 [Grade based on criteria from WHO.]
Adverse Reactions [Non-laboratory events were graded only if assessed to be possibly drug-related. Pain data were not collected.] | Gemcitabine/Cisplatin [N=67–69; all gemcitabine/cisplatin patients with laboratory or non-laboratory data.] |  |  | Etoposide/Cisplatin [N=57–63; all etoposide/cisplatin patients with laboratory or non-laboratory data.]
 | All Grades (%) | Grade 3 (%) | Grade 4 (%) | All Grades (%) | Grade 3 (%) | Grade 4 (%)
Nausea and Vomiting | 96 | 35 | 4 | 86 | 19 | 7
Alopecia | 77 | 13 | 0 | 92 | 51 | 0
Paresthesias | 38 | 0 | 0 | 16 | 2 | 0
Infection | 28 | 3 | 1 | 21 | 8 | 0
Stomatitis | 20 | 4 | 0 | 18 | 2 | 0
Diarrhea | 14 | 1 | 1 | 13 | 0 | 2
Edema [Flu-like syndrome and edema were not graded.] | 12 | - | - | 2 | - | -
Rash | 10 | 0 | 0 | 3 | 0 | 0
Hemorrhage | 9 | 0 | 3 | 3 | 0 | 3
Fever | 6 | 0 | 0 | 3 | 0 | 0
Somnolence | 3 | 0 | 0 | 3 | 2 | 0
Flu-like Syndrome | 3 | - | - | 0 | - | -
Dyspnea | 1 | 0 | 1 | 3 | 0 | 0

Table 14: Selected Laboratory Abnormalities Occurring in Patients Receiving Gemcitabine with Cisplatin in Study 4 [Grade based on criteria from WHO.]
Laboratory Abnormality [Regardless of causality.] | Gemcitabine/Cisplatin [N=67–69; all gemcitabine/cisplatin patients with laboratory or non-laboratory data.] |  |  | Etoposide/Cisplatin [N=57–63; all etoposide/cisplatin patients with laboratory or non-laboratory data.]
 | All Grades (%) | Grade 3 (%) | Grade 4 (%) | All Grades (%) | Grade 3 (%) | Grade 4 (%)
Hematologic
Anemia | 88 | 22 | 0 | 77 | 13 | 2
Neutropenia | 88 | 36 | 28 | 87 | 20 | 56
Thrombocytopenia | 81 | 39 | 16 | 45 | 8 | 5
RBC Transfusion [Percent of patients receiving transfusions. WHO Grading scale not applicable to proportion patients with transfusions.] | 29 | - | - | 21 | - | -
Platelet Transfusion | 3 | - | - | 8 | - | -
Hepatic
Increased Alkaline Phosphatase | 16 | 0 | 0 | 11 | 0 | 0
Increased ALT | 6 | 0 | 0 | 12 | 0 | 0
Increased AST | 3 | 0 | 0 | 11 | 0 | 0
Renal
Hematuria | 22 | 0 | 0 | 10 | 0 | 0
Proteinuria | 12 | 0 | 0 | 5 | 0 | 0
Increased BUN | 6 | 0 | 0 | 4 | 0 | 0
Increased Creatinine | 2 | 0 | 0 | 2 | 0 | 0

6.2 Postmarketing Experience

The following adverse reactions have been identified during post-approval use of gemcitabine. Because these reactions are reported voluntarily from a population of uncertain size, it is not always possible to reliably estimate their frequency or establish a causal relationship to drug exposure.

Blood and Lymphatic System: TMA

Cardiovascular: Congestive heart failure, myocardial infarction, arrhythmias, supraventricular arrhythmias

Vascular: Peripheral vasculitis, gangrene, capillary leak syndrome

Skin: Cellulitis; pseudocellulitis; severe cutaneous adverse reactions (SCARs), including Stevens-Johnson syndrome (SJS), toxic epidermal necrolysis (TEN), drug reaction with eosinophilia and systemic symptoms (DRESS), and acute generalized exanthematous pustulosis (AGEP); desquamation and bullous skin eruptions

Hepatic: Hepatic failure, hepatic veno-occlusive disease

Pulmonary: Interstitial pneumonitis, pulmonary fibrosis, pulmonary eosinophilia, pulmonary edema, adult respiratory distress syndrome (ARDS)

Nervous System: Posterior reversible encephalopathy syndrome (PRES)

8 USE IN SPECIFIC POPULATIONS

8.1 Pregnancy

Risk Summary

Based on animal data and its mechanism of action, Gemcitabine Injection can cause fetal harm when administered to a pregnant woman [see Clinical Pharmacology (12.1)]. There are no available data on the use of gemcitabine in pregnant women. In animal reproduction studies, gemcitabine was teratogenic, embryotoxic, and fetotoxic in mice and rabbits (see Data). Advise pregnant women of the potential risk to a fetus [see Use in Specific Populations (8.3)].

In the U.S. general population, the estimated background risk of major birth defects and miscarriages in clinically recognized pregnancies is 2–4% and 15–20%, respectively.

Data

Animal Data

Gemcitabine is embryotoxic in mice. Daily dosing of gemcitabine to pregnant mice increased the incidence of fetal malformations (cleft palate, incomplete ossification) at doses of 1.5 mg/kg/day [about 0.005 times the 1000 mg/m^2 clinical dose based on body surface area (BSA)]. Gemcitabine is embryotoxic and fetotoxic in rabbits. Daily dosing of gemcitabine to pregnant rabbits resulted in fetotoxicity (decreased fetal viability, reduced litter sizes and developmental delays) and increased the incidence of fetal malformations (fused pulmonary artery, absence of gall bladder) at doses of 0.1 mg/kg/day (about 0.002 times the 1000 mg/m^2 clinical dose based on BSA).

8.2 Lactation

Risk Summary

There is no information regarding the presence of gemcitabine or its metabolites in human milk, or their effects on the breastfed infant or on milk production. Due to the potential for serious adverse reactions in breastfed infants, advise women not to breastfeed during treatment with Gemcitabine Injection and for at least one week following the last dose.

8.3 Females and Males of Reproductive Potential

Pregnancy Testing

Verify pregnancy status in females of reproductive potential prior to initiating Gemcitabine Injection [see Use in Specific Populations (8.1)].

Contraception

Gemcitabine Injection can cause fetal harm when administered to a pregnant woman [see Use in Specific Populations (8.1)].

Females

Because of the potential for genotoxicity, advise females of reproductive potential to use effective contraception during treatment with Gemcitabine Injection and for 6 months after the final dose.

Males

Because of the potential for genotoxicity, advise males with female partners of reproductive potential to use effective contraception during treatment with Gemcitabine Injection and for 3 months after the final dose [see Nonclinical Toxicology (13.1)].

Infertility

Males

Based on animal studies, gemcitabine may impair fertility in males of reproductive potential [see Nonclinical Toxicology (13.1)]. It is not known whether these effects on fertility are reversible.

8.4 Pediatric Use

The safety and effectiveness of gemcitabine have not been established in pediatric patients.

The safety and pharmacokinetics of gemcitabine were evaluated in a trial in pediatric patients with refractory leukemia. The maximum tolerated dose was 10 mg/m^2/min for 360 minutes weekly for three weeks followed by a one-week rest period.

The safety and activity of gemcitabine were evaluated in a trial of pediatric patients with relapsed acute lymphoblastic leukemia (22 patients) and acute myelogenous leukemia (10 patients) at a dose of 10 mg/m^2/min administered over 360 minutes weekly for three weeks followed by a one-week rest period. Patients with M1 or M2 bone marrow on Day 28 who did not experience unacceptable toxicity were eligible to receive a maximum of one additional four-week course. Toxicities observed included myelosuppression, febrile neutropenia, increased serum transaminases, nausea, and rash/desquamation. No meaningful clinical activity was observed in this trial.

8.5 Geriatric Use

In clinical studies which enrolled 979 patients with various malignancies who received single agent gemcitabine, no overall differences in safety were observed between patients aged 65 and older and younger patients, with the exception of a higher rate of Grade 3–4 thrombocytopenia in older patients as compared to younger patients.

In a randomized trial in women with ovarian cancer (Study 1), 175 women received gemcitabine with carboplatin, of which 29% were age 65 years or older. Similar effectiveness was observed between older and younger women. There was significantly higher Grade 3–4 neutropenia in women 65 years of age or older [see Dosage and Administration (2.1)].

Gemcitabine clearance is affected by age; however, there are no recommended dose adjustments based on patients' age [see Clinical Pharmacology (12.3)].

8.6 Gender

Gemcitabine clearance is decreased in females [see Clinical Pharmacology (12.3)]. In single agent studies of gemcitabine, women, especially older women, were more likely not to proceed to a subsequent cycle and to experience Grade 3–4 neutropenia and thrombocytopenia [see Dosage and Administration (2.1, 2.2, 2.3, 2.4)].

10 OVERDOSAGE

There is no known antidote for overdoses of gemcitabine. Myelosuppression, paresthesias, and severe rash were the principal toxicities seen when a single dose as high as 5700 mg/m^2 was administered by intravenous infusion over 30 minutes every 2 weeks to several patients in a dose-escalation study. In the event of suspected overdose, monitor with appropriate blood counts and provide supportive therapy, as necessary.

11 DESCRIPTION

Gemcitabine is a nucleoside metabolic inhibitor. The chemical name of gemcitabine HCl is 2´-deoxy-2´,2´-difluorocytidine monohydrochloride (β-isomer). The structural formula is as follows:

Gemcitabine HCl is a white to off-white solid with a molecular formula of C9H11F2N3O4 ∙ HCl and a molecular weight of 299.66 g/mol. It is soluble in water, slightly soluble in methanol, and practically insoluble in ethanol and polar organic solvents.

Gemcitabine Injection is a sterile solution in single-dose vials for intravenous use. Each vial contains 200 mg, 1 g, or 2 g of gemcitabine equivalent to 227.7 mg, 1.139 g, or 2.227 g of gemcitabine HCl. Each mL contains 38 mg of gemcitabine free base in Water for Injection equivalent to 43.27 mg of gemcitabine HCl. Hydrochloric acid and/or sodium hydroxide may have been added for pH adjustment.

12 CLINICAL PHARMACOLOGY

12.1 Mechanism of Action

Gemcitabine kills cells undergoing DNA synthesis and blocks the progression of cells through the G1/S-phase boundary. Gemcitabine is metabolized by nucleoside kinases to diphosphate (dFdCDP) and triphosphate (dFdCTP) nucleosides. Gemcitabine diphosphate inhibits ribonucleotide reductase, an enzyme responsible for catalyzing the reactions that generate deoxynucleoside triphosphates for DNA synthesis, resulting in reductions in deoxynucleotide concentrations, including dCTP. Gemcitabine triphosphate competes with dCTP for incorporation into DNA. The reduction in the intracellular concentration of dCTP by the action of the diphosphate enhances the incorporation of gemcitabine triphosphate into DNA (self-potentiation). After the gemcitabine nucleotide is incorporated into DNA, only one additional nucleotide is added to the growing DNA strands which eventually results in the initiation of apoptotic cell death.

12.3 Pharmacokinetics

The pharmacokinetics of gemcitabine were examined in 353 patients, with various solid tumors. Pharmacokinetic parameters were derived using data from patients treated for varying durations of therapy given weekly with periodic rest weeks and using both short infusions (<70 minutes) and long infusions (70 to 285 minutes). The total gemcitabine dose varied from 500 mg/m^2 to 3600 mg/m^2.

Distribution

The volume of distribution was increased with infusion length. Volume of distribution of gemcitabine was 50 L/m^2 following infusions lasting <70 minutes. For long infusions, the volume of distribution rose to 370 L/m^2.

Gemcitabine pharmacokinetics are linear and are described by a 2-compartment model. Population pharmacokinetic analyses of combined single and multiple dose studies showed that the volume of distribution of gemcitabine was significantly influenced by duration of infusion and sex. Gemcitabine plasma protein binding is negligible.

Elimination

Metabolism

The active metabolite, gemcitabine triphosphate, can be extracted from peripheral blood mononuclear cells. The half-life of the terminal phase for gemcitabine triphosphate from mononuclear cells ranges from 1.7 to 19.4 hours.

Excretion

Gemcitabine disposition was studied in 5 patients who received a single 1000 mg/m^2 of radiolabeled drug as a 30-minute infusion. Within one (1) week, 92% to 98% of the dose was recovered, almost entirely in the urine. Gemcitabine (<10%) and the inactive uracil metabolite, 2´-deoxy-2´,2´-difluorouridine (dFdU), accounted for 99% of the excreted dose. The metabolite dFdU is also found in plasma.

Specific Populations

Geriatric Patients

Clearance of gemcitabine was affected by age. The lower clearance in geriatric patients results in higher concentrations of gemcitabine for any given dose. Differences in either clearance or volume of distribution based on patient characteristics or the duration of infusion result in changes in half-life and plasma concentrations. Table 15 shows plasma clearance and half-life of gemcitabine following short infusions for typical patients by age and sex.

Gemcitabine half-life for short infusions ranged from 42 to 94 minutes, and for long infusions varied from 245 to 638 minutes, depending on age and sex, reflecting a greatly increased volume of distribution with longer infusions.

Male and Female Patients

Females have lower clearance and longer half-lives than male patients as described in Table 15.

Table 15: Gemcitabine Clearance and Half-Life for the "Typical" Patient
Age | Clearance Men (L/hr/m^2) | Clearance Women (L/hr/m^2) | Half-Life [Half-life for patients receiving a <70 minute infusion.] Men (min) | Half-Life Women (min)
29 | 92.2 | 69.4 | 42 | 49
45 | 75.7 | 57.0 | 48 | 57
65 | 55.1 | 41.5 | 61 | 73
79 | 40.7 | 30.7 | 79 | 94

Patients with Renal Impairment

No clinical studies have been conducted with gemcitabine in patients with decreased renal function.

Patients with Hepatic Impairment

No clinical studies have been conducted with gemcitabine in patients with decreased hepatic function.

Drug Interaction Studies

When gemcitabine (1250 mg/m^2 on Days 1 and 8) and cisplatin (75 mg/m^2 on Day 1) were administered in patients with NSCLC, the clearance of gemcitabine on Day 1 was 128 L/hr/m^2 and on Day 8 was 107 L/hr/m^2. Data from patients with NSCLC demonstrate that gemcitabine and carboplatin given in combination does not alter the pharmacokinetics of gemcitabine or carboplatin compared to administration of either single agent, however, due to wide confidence intervals and small sample size, interpatient variability may be observed.

Data from patients with metastatic breast cancer shows that gemcitabine has little or no effect on the pharmacokinetics (clearance and half-life) of paclitaxel and paclitaxel has little or no effect on the pharmacokinetics of gemcitabine.

13 NONCLINICAL TOXICOLOGY

13.1 Carcinogenesis, Mutagenesis, Impairment of Fertility

Long-term animal studies to evaluate the carcinogenic potential of gemcitabine have not been conducted. Gemcitabine was mutagenic in an in vitro mouse lymphoma (L5178Y) assay and was clastogenic in an in vivo mouse micronucleus assay. Gemcitabine intraperitoneal doses of 0.5 mg/kg/day (about 1/700 the 1000 mg/m^2 clinical dose based on BSA) in male mice resulted in moderate to severe hypospermatogenesis, decreased fertility, and decreased implantations. In female mice, fertility was not affected but maternal toxicities were observed at 1.5 mg/kg/day administered intravenously (about 1/200 the 1000 mg/m^2 clinical dose based on BSA) and fetotoxicity or embryolethality was observed at 0.25 mg/kg/day administered intravenously (about 1/1300 the 1000 mg/m^2 clinical dose based on BSA).

14 CLINICAL STUDIES

14.1 Ovarian Cancer

The efficacy of gemcitabine was evaluated in a randomized trial (Study 1) conducted in women with advanced ovarian cancer that had relapsed at least 6 months after first-line platinum-based therapy. Patients were randomized to receive either gemcitabine 1000 mg/m^2 on Days 1 and 8 of each 21-day cycle with carboplatin AUC 4 on Day 1 after gemcitabine administration (n = 178) or carboplatin AUC 5 on Day 1 of each 21-day cycle (n = 178). The major efficacy outcome measure was progression-free survival (PFS).

A total of 356 patients were enrolled. Demographics and baseline characteristics are shown in Table 16. Efficacy results are presented in Table 17 and Figure 1. The addition of gemcitabine to carboplatin resulted in statistically significant improvements in PFS and overall response rate. Approximately 75% of patients in each arm received additional chemotherapy for disease progression; 13 of 120 patients in the carboplatin alone arm received gemcitabine for treatment of disease progression. There was no significant difference in overall survival between the treatment arms.

Table 16: Baseline Demographics and Clinical Characteristics for Study 1
 | Gemcitabine/Carboplatin (N=178) | Carboplatin (N=178)
Median age, years | 59 | 58
Range | 36 to 78 | 21 to 81
Baseline ECOG performance status 0–1 [5 patients on gemcitabine/carboplatin arm and 4 patients on carboplatin arm had no baseline Eastern Cooperative Oncology Group (ECOG) performance status.] | 94% | 95%
Disease Status
Evaluable | 8% | 3%
Bidimensionally measurable | 92% | 96%
Platinum-free interval [2 patients on gemcitabine/carboplatin arm and 1 patient on carboplatin arm had platinum-free interval <6 months.]
6–12 months | 40% | 40%
>12 months | 59% | 60%
First-line therapy
Platinum-taxane combination | 70% | 71%
Platinum-non-taxane combination | 29% | 28%
Platinum monotherapy | 1% | 1%

Table 17: Efficacy Results in Study 1
Efficacy Parameter | Gemcitabine/Carboplatin (N=178) | Carboplatin (N=178)
Progression-Free Survival
Median (95% CI [CI=confidence interval.]) in months | 8.6 (8.0, 9.7) | 5.8 (5.2, 7.1)
Hazard Ratio (95% CI) | 0.72 (0.57, 0.90)
p=value [Log rank, unadjusted.] | p=0.0038
Overall Survival
Median (95% CI) in months | 18.0 (16.2, 20.3) | 17.3 (15.2, 19.3)
Hazard Ratio (95% CI) | 0.98 (0.78, 1.24)
p=value | p=0.8977
Overall Response Rate by Investigator Review | 47.2% | 30.9%
p=value [Chi square.] | p=0.0016
CR [CR=Complete response] | 14.6% | 6.2%
PR with PRNM [PR with PRNM=Partial response with partial response, non-measurable disease] | 32.6% | 24.7%
Overall Response Rate by Independent Review [Independently reviewed cohort - gemcitabine/carboplatin (n=121), carboplatin (n=101); independent reviewers unable to measure disease detected by sonography or physical exam.] | 46.3% | 35.6%
p=value | p=0.11
CR | 9.1% | 4.0%
PR with PRNM | 37.2% | 31.7%

Figure 1: Kaplan-Meier Curves for Progression-Free Survival in Study 1

14.2 Breast Cancer

The efficacy of gemcitabine was evaluated in a multinational, randomized, open-label trial conducted in women receiving initial treatment for metastatic breast cancer and who have received prior adjuvant/neoadjuvant anthracycline chemotherapy unless clinically contraindicated.

Patients were randomized to receive gemcitabine 1250 mg/m^2 on Days 1 and 8 of each 21-day cycle with paclitaxel 175 mg/m^2 administered on Day 1 before gemcitabine administration (n = 267) or paclitaxel 175 mg/m^2 on Day 1 of each 21-day cycle (n = 262). The major efficacy outcome measure was time to documented disease progression.

A total of 529 patients were enrolled. Demographic and baseline characteristics were similar between treatment arms (Table 18).

Efficacy results are presented in Table 19 and Figure 2. The addition of gemcitabine to paclitaxel resulted in statistically significant improvement in time to documented disease progression and overall response rate compared to paclitaxel alone. There was no significant difference in overall survival.

Table 18: Baseline Demographics and Clinical Characteristics for Study 2
 | Gemcitabine/Paclitaxel (N=267) | Paclitaxel (N=262)
Median age, years | 53 | 52
Range | 26 to 83 | 26 to 75
Metastatic disease | 97% | 97%
Baseline KPS [Karnofsky Performance Status.] ≥90 | 70% | 74%
Number of tumor sites
1–2 | 57% | 59%
≥3 | 43% | 41%
Visceral disease | 73% | 73%
Prior anthracycline | 97% | 96%

Table 19: Efficacy Results in Study 2
Efficacy Parameter | Gemcitabine/Paclitaxel (N=267) | Paclitaxel (N=262)
Time to Documented Disease Progression [These represent reconciliation of investigator and Independent Review Committee assessments according to a predefined algorithm.]
Median (95% CI) in months | 5.2 (4.2, 5.6) | 2.9 (2.6, 3.7)
Hazard Ratio (95% CI) | 0.650 (0.524, 0.805)
p-value | p<0.0001
Overall Survival [Based on the ITT population.]
Median (95% CI) in months | 18.6 (16.5, 20.7) | 15.8 (14.1, 17.3)
Hazard Ratio (95% CI) | 0.86 (0.71, 1.04)
p-value | Not Significant
Overall Response Rate (95% CI) | 40.8% (34.9, 46.7) | 22.1% (17.1, 27.2)
p-value | p<0.0001

Figure 2: Kaplan-Meier Curves for Time to Documented Disease Progression in Study 2

14.3 Non-Small Cell Lung Cancer

The efficacy of gemcitabine was evaluated in two randomized, multicenter trials.

Study 3: 28-Day Schedule

A multinational, randomized trial (Study 3) compared gemcitabine with cisplatin to cisplatin alone in the treatment of patients with inoperable Stage IIIA, IIIB, or IV NSCLC who had not received prior chemotherapy. Patients were randomized to receive either gemcitabine 1000 mg/m^2 on Days 1, 8, and 15 of each 28-day cycle with cisplatin 100 mg/m^2 on Day 1 after gemcitabine administration (N=260) or cisplatin 100 mg/m^2 on Day 1 of each 28-day cycle (N=262). The major efficacy outcome measure was overall survival.

A total of 522 patients were enrolled. Demographics and baseline characteristics (Table 20) were similar between arms with the exception of histologic subtype of NSCLC, with 48% of patients on the cisplatin arm and 37% of patients on the gemcitabine with cisplatin arm having adenocarcinoma.

Efficacy results are presented in Table 21 and Figure 3.

Study 4: 21-Day Schedule

A randomized (1:1), multicenter trial (Study 4) was conducted in patients with Stage IIIB or IV NSCLC. Patients were randomized to receive gemcitabine 1250 mg/m^2 on Days 1 and 8 of each 21-day cycle with cisplatin 100 mg/m^2 on Day 1 after gemcitabine administration or etoposide 100 mg/m^2 intravenously on Days 1, 2, and 3 with cisplatin 100 mg/m^2 on Day 1 of each 21-day cycle. The major efficacy outcome measure was response rate.

A total of 135 patients were enrolled. Demographics and baseline characteristics are summarized in Table 20.

Efficacy results are presented in Table 21. There was no significant difference in survival between the two treatment arms. The median survival was 8.7 months for the gemcitabine with cisplatin arm versus 7 months for the etoposide with cisplatin arm. Median time to disease progression for the gemcitabine with cisplatin arm was 5 months compared to 4.1 months on the etoposide with cisplatin arm (Log rank p=0.015, two-sided). The objective response rate for the gemcitabine with cisplatin arm was 33% compared to 14% on the etoposide with cisplatin arm (Fisher's Exact p=0.01, two-sided).

Figure 3: Kaplan-Meier Curves for Overall Survival in Study 3

Table 20: Baseline Demographics and Clinical Characteristics for Studies 3 and 4
Trial | 28-day Schedule (Study 3) |  | 21-day Schedule (Study 4)
 | Gemcitabine/Cisplatin (N=260) | Cisplatin (N=262) | Gemcitabine/Cisplatin (N=69) | Etoposide/Cisplatin (N=66)
Male | 70% | 71% | 93% | 92%
Median age, years | 62 | 63 | 58 | 60
Range | 36 to 88 | 35 to 79 | 33 to 76 | 35 to 75
Stage IIIA | 7% | 7% | N/A [N/A Not applicable.] | N/A
Stage IIIB | 26% | 23% | 48% | 52%
Stage IV | 67% | 70% | 52% | 49%
Baseline KPS [Karnofsky Performance Status.] 70 to 80 | 41% | 44% | 45% | 52%
Baseline KPS 90 to 100 | 57% | 55% | 55% | 49%

Table 21: Efficacy Results for Studies 3 and 4
Trial | 28-day Schedule (Study 3) |  | 21-day Schedule (Study 4)
Efficacy Parameter | Gemcitabine/Cisplatin (N=260) | Cisplatin (N=262) | Gemcitabine/Cisplatin (N=69) | Etoposide/Cisplatin (N=66)
Survival
Median (95% CI [CI=confidence intervals.]) in months | 9.0 (8.2, 11.0) | 7.6 (6.6, 8.8) | 8.7 (7.8, 10.1) | 7.0 (6.0, 9.7)
p-value [p-value two-sided Fisher's Exact test for difference in binomial proportions; log rank test for time-to-event analyses.] | p=0.008 |  | p=0.18
Time to Disease Progression
Median (95% CI) in months | 5.2 (4.2, 5.7) | 3.7 (3.0, 4.3) | 5.0 (4.2, 6.4) | 4.1 (2.4, 4.5)
p-value | p=0.009 |  | p=0.015
Tumor Response | 26% | 10% | 33% | 14%
p-value | p<0.0001 |  | p=0.01

14.4 Pancreatic Cancer

The efficacy of gemcitabine was evaluated in two trials (Studies 5 and 6), a randomized, single-blind, two-arm, active-controlled trial (Study 5) conducted in patients with locally advanced or metastatic pancreatic cancer who had received no prior chemotherapy and in a single-arm, open-label, multicenter trial (Study 6) conducted in patients with locally advanced or metastatic pancreatic cancer previously treated with fluorouracil or a fluorouracil-containing regimen. In Study 5, patients were randomized to receive either gemcitabine 1000 mg/m^2 intravenously over 30 minutes once weekly for 7 weeks followed by a one-week rest, then once weekly for 3 consecutive weeks every 28-days in subsequent cycles (n=63) or fluorouracil 600 mg/m^2 intravenously over 30 minutes once weekly (n=63). In Study 6, all patients received gemcitabine 1000 mg/m^2 intravenously over 30 minutes once weekly for 7 weeks followed by a one-week rest, then once weekly for 3 consecutive weeks every 28-days in subsequent cycles.

The major efficacy outcome measure in both trials was "clinical benefit response". A patient was considered to have had a clinical benefit response if either of the following occurred:

- The patient achieved a ≥50% reduction in pain intensity (Memorial Pain Assessment Card) or analgesic consumption, or a 20-point or greater improvement in performance status (Karnofsky Performance Status) for a period of at least 4 consecutive weeks, without showing any sustained worsening in any of the other parameters. Sustained worsening was defined as 4 consecutive weeks with either any increase in pain intensity or analgesic consumption or a 20-point decrease in performance status occurring during the first 12 weeks of therapy.

OR

- The patient was stable on all of the aforementioned parameters, and showed a marked, sustained weight gain (≥7% increase maintained for ≥4 weeks) not due to fluid accumulation.

Study 5 enrolled 126 patients. Demographics and baseline characteristics were similar between the arms (Table 22).

The efficacy results are shown in Table 23 and Figure 4. Patients treated with gemcitabine had statistically significant increases in clinical benefit response, survival, and time to disease progression compared to those randomized to receive fluorouracil. No confirmed objective tumor responses were observed in either treatment arm.

Table 22: Baseline Demographics and Clinical Characteristics for Study 5
 | Gemcitabine (N=63) | Fluorouracil (N=63)
Male | 54% | 54%
Median age | 62 years | 61 years
Range | 37 to 79 | 36 to 77
Stage IV disease | 71% | 76%
Baseline KPS [Karnofsky Performance Status.] ≤70 | 70% | 68%

Table 23: Efficacy Results in Study 5
Efficacy Parameter | Gemcitabine (N=63) | Fluorouracil (N=63)
Clinical Benefit Response | 22.2% | 4.8%
p-value [p-value for clinical benefit response calculated using the two-sided test for difference in binomial proportions. All other p-values are calculated using log rank test.] | p=0.004
Overall Survival
Median (95% CI) in months | 5.7 (4.7, 6.9) | 4.2 (3.1, 5.1)
p-value | p=0.0009
Time to Disease Progression
Median (95% CI) in months | 2.1 (1.9, 3.4) | 0.9 (0.9, 1.1)
p-value | p=0.0013

Figure 4: Kaplan-Meier Curves for Overall Survival in Study 5

15 REFERENCES

1. “OSHA Hazardous Drugs.” OSHA. http://www.osha.gov/SLTC/hazardousdrugs/index.html

16 HOW SUPPLIED/STORAGE AND HANDLING

Gemcitabine Injection appears as a clear and colorless to light straw-colored solution. It is available in sterile single-dose vials individually packaged in a carton as follows:

- 200 mg/5.26 mL (38 mg/mL), sterile solution in a single-dose glass vial per package, NDC 0409-0183-01
- 1 g/26.3 mL (38 mg/mL), sterile solution in a single-dose glass vial per package, NDC 0409-0181-01
- 2 g/52.6 mL (38 mg/mL), sterile solution in a single-dose glass vial per package, NDC 0409-0182-01

STORAGE AND HANDLING

Store at 2° to 8°C (36° to 46°F). Do not freeze.

Gemcitabine Injection is a cytotoxic drug. Follow applicable special handling and disposal procedures.^1

17 PATIENT COUNSELING INFORMATION

Myelosuppression

Advise patients of the risks of myelosuppression. Instruct patients to immediately contact their healthcare provider should any signs or symptoms of infection, including fever, or if bleeding, or signs of anemia, occur [see Warnings and Precautions (5.2)].

Severe Cutaneous Adverse Reactions (SCARs)

Advise patients of the risks of SCARs, including Stevens-Johnson syndrome (SJS), toxic epidermal necrolysis (TEN), drug reaction with eosinophilia and systemic symptoms (DRESS), and acute generalized exanthematous pustulosis (AGEP). Instruct patients to immediately contact their healthcare provider should any signs or symptoms of severe skin rash or skin peeling, blistering and/or mouth sores occur [see Warnings and Precautions (5.3)].

Pulmonary Toxicity

Advise patients of the risks of pulmonary toxicity including respiratory failure and death. Instruct patients to immediately contact their healthcare provider for development of shortness of breath, wheezing, or cough [see Warnings and Precautions (5.4)].

Hemolytic Uremic Syndrome and Renal Failure

Advise patients of the risks of hemolytic uremic syndrome and associated renal failure. Instruct patients to immediately contact their healthcare provider for changes in the color or volume of urine output or for increased bruising or bleeding [see Warnings and Precautions (5.5)].

Hepatic Toxicity

Advise patients of the risks of hepatic toxicity including liver failure and death. Instruct patients to immediately contact their healthcare provider for signs of jaundice or for pain/tenderness in the right upper abdominal quadrant [see Warnings and Precautions (5.6)].

Embryo-Fetal Toxicity

Advise females and males of reproductive potential that Gemcitabine Injection can cause fetal harm. Advise females of reproductive potential to use effective contraception during treatment with Gemcitabine Injection and for 6 months after the final dose. Advise male patients with female partners of reproductive potential to use effective contraception during treatment with Gemcitabine Injection and for 3 months after the final dose [see Warnings and Precaution (5.7), Use in Specific Populations (8.1, 8.3)].

Lactation

Advise women not to breastfeed during treatment with Gemcitabine Injection and for at least one week after the last dose [see Use in Specific Populations (8.2)].

Infertility

Advise males of reproductive potential of the potential for reduced fertility with Gemcitabine Injection [see Use in Specific Populations (8.3), Nonclinical Toxicology (13.1)].

This product’s labeling may have been updated. For the most recent prescribing information, please visit www.pfizer.com.

Distributed by Hospira, Inc. Lake Forest, IL 60045 USA

LAB-1029-6.0

PRINCIPAL DISPLAY PANEL - 1 g/26.3 mL Vial Label

Gemcitabine Injection

1 g/26.3 mL

(38 mg/mL)

For Intravenous Use
Must Be Diluted Before Use
Store at 2 to 8°C (36 to 46°F)
26.3 mL Single-dose Vial.
Discard unused portion.

PRINCIPAL DISPLAY PANEL - 1 g/26.3 mL Vial Carton

Rx only
NDC 0409-0181-01

Gemcitabine
Injection

1 g/26.3 mL

(38 mg/mL)

For Intravenous Use
Must Be Diluted Before Use
Store at 2 to 8°C (36 to 46°F)
26.3 mL Single-dose Vial
Discard Unused Portion

Caution: Cytotoxic Agent

PRINCIPAL DISPLAY PANEL - 200 mg/5.26 mL Vial Label

Gemcitabine Injection

200 mg/5.26 mL

(38 mg/mL)

For Intravenous Use
Must Be Diluted Before Use
Store at 2 to 8°C (36 to 46°F)
5.26 mL Single-dose Vial.
Discard unused portion.

PRINCIPAL DISPLAY PANEL - 200 mg/5.26 mL Vial Carton

Rx only
NDC 0409-0183-01

Gemcitabine
Injection

200 mg/5.26 mL

(38 mg/mL)

For Intravenous Use
Must Be Diluted Before Use
Store at 2 to 8°C (36 to 46°F)
5.26 mL Single-dose Vial
Discard Unused Portion

Caution: Cytotoxic Agent

PRINCIPAL DISPLAY PANEL - 2 g/52.6 mL Vial Label

Gemcitabine Injection

2 g/52.6 mL

(38 mg/mL)

For Intravenous Use
Must Be Diluted Before Use
Store at 2 to 8°C (36 to 46°F)
52.6 mL Single-dose Vial.
Discard unused portion.

PRINCIPAL DISPLAY PANEL - 2 g/52.6 mL Vial Carton

Rx only
NDC 0409-0182-01

Gemcitabine
Injection

2 g/52.6 mL

(38 mg/mL)

For Intravenous Use
Must Be Diluted Before Use
Store at 2 to 8°C (36 to 46°F)
52.6 mL Single-dose Vial
Discard Unused Portion

Caution: Cytotoxic Agent